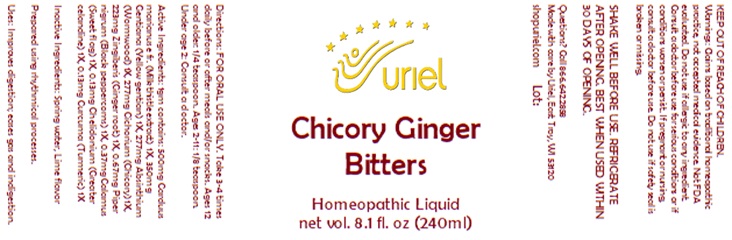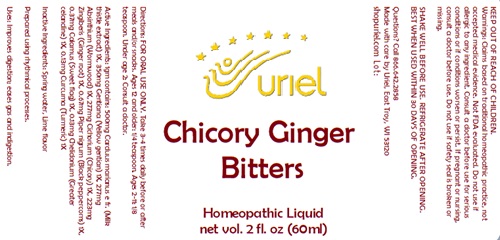 DRUG LABEL: Chicory Ginger Bitters
NDC: 48951-3251 | Form: LIQUID
Manufacturer: Uriel Pharmacy, Inc.
Category: homeopathic | Type: HUMAN OTC DRUG LABEL
Date: 20251120

ACTIVE INGREDIENTS: BLACK PEPPER 1 [hp_X]/1 mL; CHELIDONIUM MAJUS 1 [hp_X]/1 mL; MILK THISTLE 1 [hp_X]/1 mL; WORMWOOD 1 [hp_X]/1 mL; CICHORIUM INTYBUS WHOLE 1 [hp_X]/1 mL; ACORUS CALAMUS ROOT 1 [hp_X]/1 mL; TURMERIC 1 [hp_X]/1 mL; GENTIANA LUTEA ROOT 1 [hp_X]/1 mL; GINGER 1 [hp_X]/1 mL
INACTIVE INGREDIENTS: LIME OIL; WATER

Chicory Ginger Bitters

INDICATIONS AND USAGE

Directions: FOR ORAL USE ONLY.

DOSAGE AND ADMINISTRATION

Take 3-4 times daily before or after meals and/or snacks. Ages 12 and older: 1/4 teaspoon. Ages 2-11: 1/8 teaspoon. Under age 2: Consult a doctor.

ACTIVE INGREDIENT

Active Ingredients: 1gm contains: 500mg Carduus marianus (Milk thistle seeds) 1X, 350mg Gentiana (Yellow gentian) 1X, 277mg Absinthium (Wormwood) 1X, 277mg Cichorium (Chicory) 1X, 223mg Zingiberis (Ginger root) 1X, 0.67mg Piper nigrum (Black peppercorns) 1X, 0.37mg Calamus (Sweet flag) 1X, 0.13mg Chelidonium (Greater celandine) 1X, 0.13mg Curcuma (Turmeric) 1X

Inactive Ingredients: Distilled water, Lime flavor

"prepared using rhythmical processes"

PURPOSE

Uses: Improves digestion; eases gas and indigestion.

KEEP OUT OF REACH OF CHILDREN.

WARNINGS

Warnings: Claims based on traditional homeopathic practice, not accepted medical evidence. Not FDA evaluated. Do not use if allergic to any ingredient. Consult a doctor before use for serious conditions or if conditions worsen or persist. If pregnant or nursing, consult a doctor before use. Do not use if safety seal is broken or missing.

SHAKE WELL BEFORE USE. REFRIGERATE AFTER OPENING. BEST WHEN USED WITHIN 30 DAYS OF OPENING.

Questions? Call 866.642.2858
Made with care by Uriel, East Troy, WI 53120
shopuriel.com Lot: